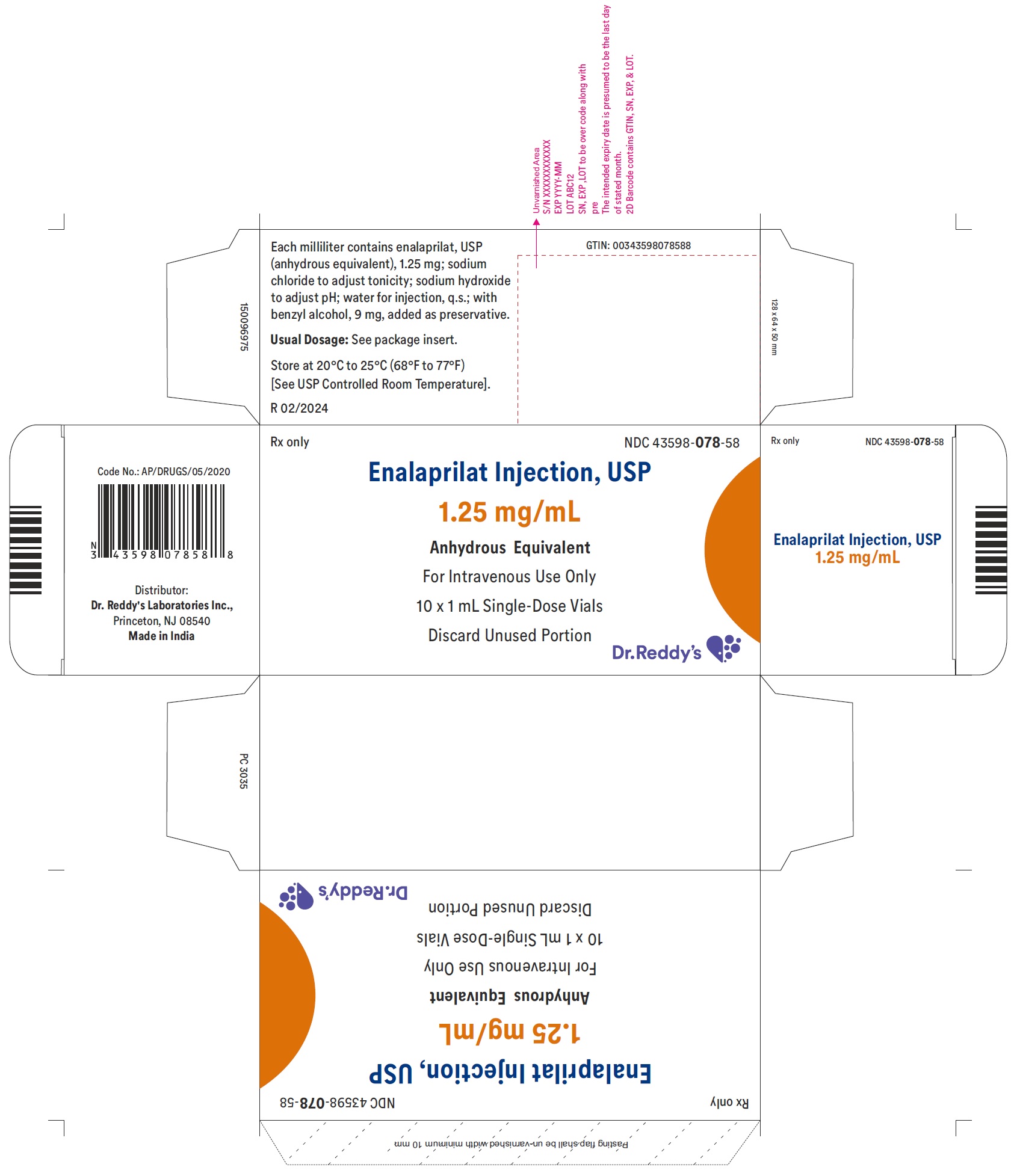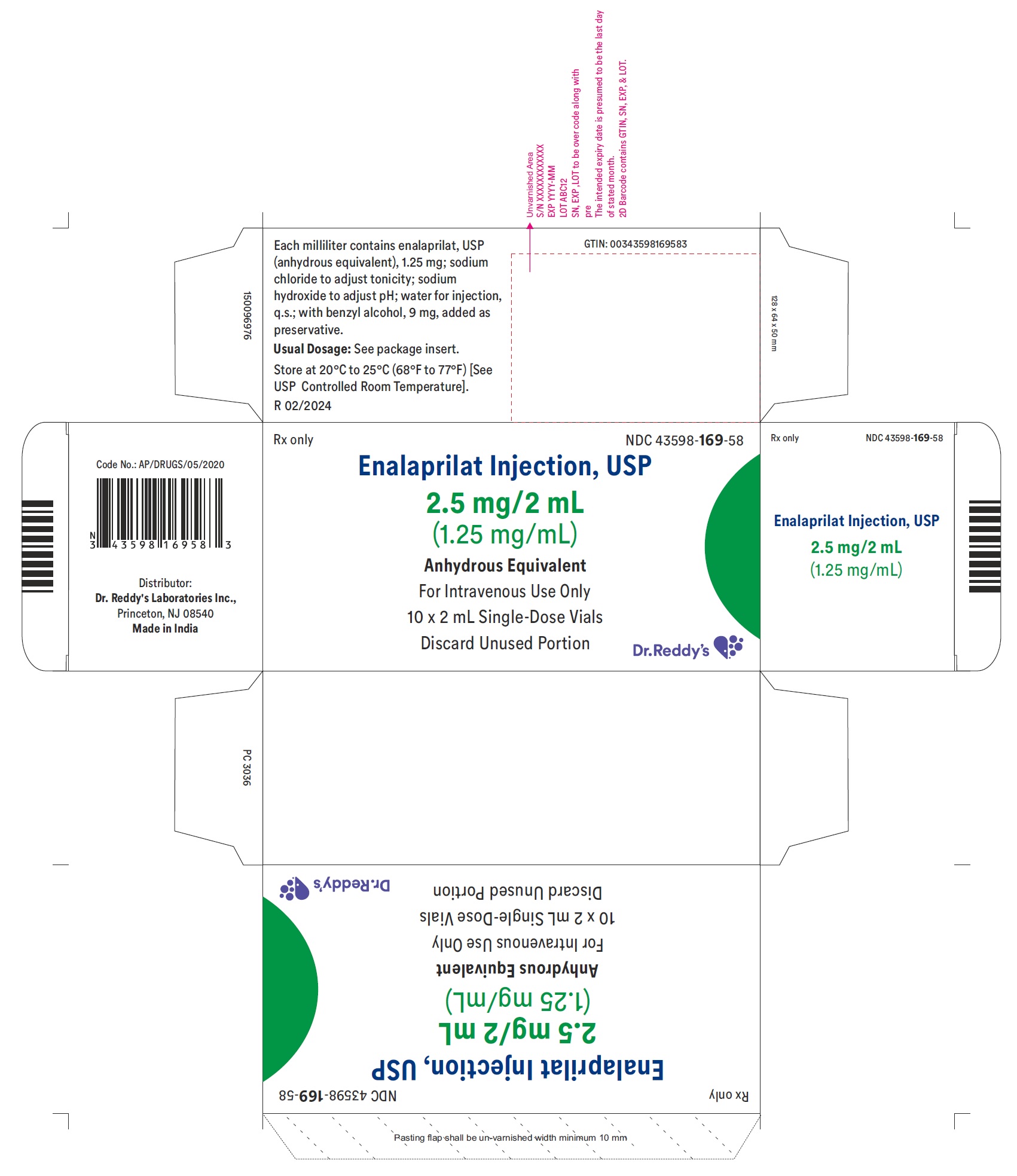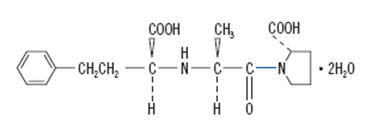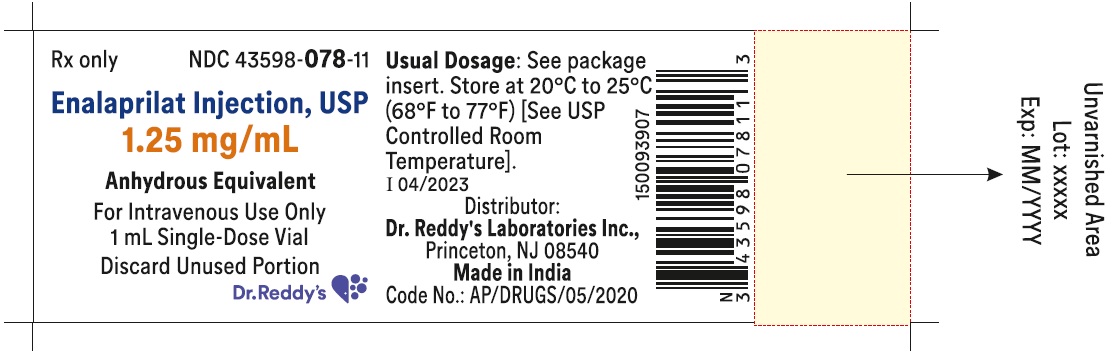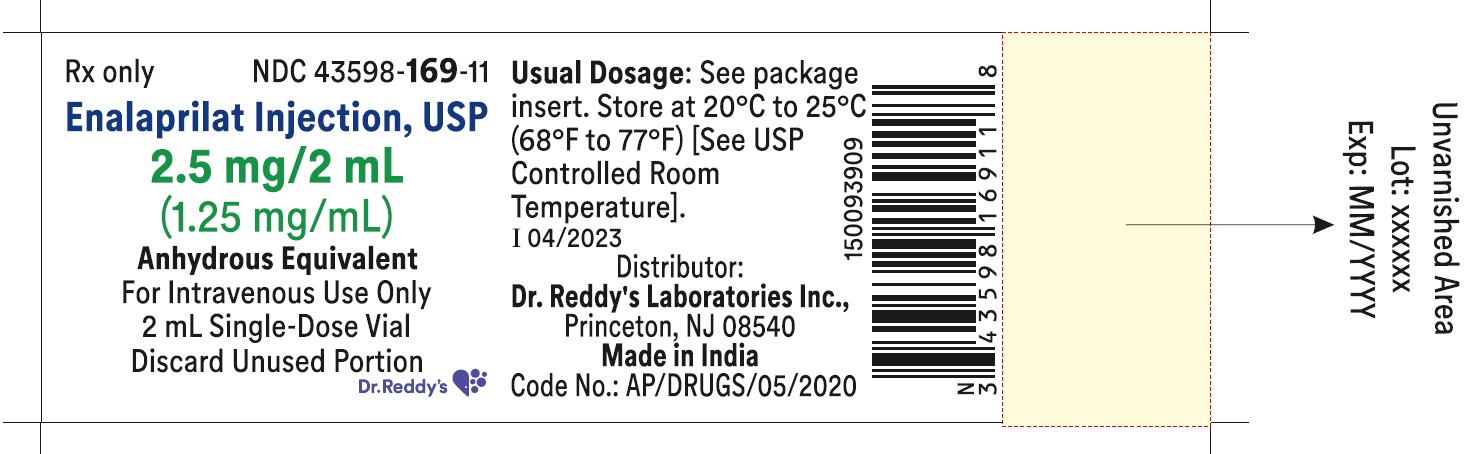 DRUG LABEL: Enalaprilat
NDC: 43598-078 | Form: INJECTION
Manufacturer: Dr. Reddys Laboratories Inc
Category: prescription | Type: HUMAN PRESCRIPTION DRUG LABEL
Date: 20240607

ACTIVE INGREDIENTS: ENALAPRILAT 1.25 mg/1 mL
INACTIVE INGREDIENTS: SODIUM CHLORIDE; SODIUM HYDROXIDE; WATER; BENZYL ALCOHOL

Enalaprilat Injection USP

Rx only

BOXED WARNING

USE IN PREGNANCY

When used in pregnancy during the second and third trimesters, ACE inhibitors can cause injury and even death to the developing fetus. When pregnancy is detected, enalaprilat injection should be discontinued as soon as possible. See WARNINGS, Fetal/Neonatal Morbidity and Mortality.

DESCRIPTION

Enalaprilat injection, USP is a sterile aqueous solution for intravenous administration. Enalaprilat is an angiotensin-converting enzyme inhibitor. It is chemically described as (S)-1-[N-(1-carboxy-3-phenylpropyl)-L-alanyl]-L-proline dihydrate. Its molecular formula is C18H24N2O5•2H2O and its structural formula is:

Enalaprilat, USP is a white or almost white crystalline powder with a molecular weight of 384.43. It is sparingly soluble in methanol and slightly soluble in water.

Each milliliter of enalaprilat injection, USP contains 1.25 mg enalaprilat, USP (anhydrous equivalent); sodium chloride to adjust tonicity; sodium hydroxide to adjust pH; water for injection, q.s.; with benzyl alcohol, 9 mg, added as a preservative.

CLINICAL PHARMACOLOGY

Enalaprilat, an angiotensin-converting enzyme (ACE) inhibitor when administered intravenously, is the active metabolite of the orally administered pro-drug, enalapril maleate. Enalaprilat is poorly absorbed orally.

Mechanism of Action

Intravenous enalaprilat, or oral enalapril, after hydrolysis to enalaprilat, inhibits ACE in human subjects and animals. ACE is a peptidyl dipeptidase that catalyzes the conversion of angiotensin I to the vasoconstrictor substance, angiotensin II. Angiotensin II also stimulates aldosterone secretion by the adrenal cortex. Inhibition of ACE results in decreased plasma angiotensin II, which leads to decreased vasopressor activity and to decreased aldosterone secretion. Although the latter decrease is small, it results in small increases of serum potassium. In hypertensive patients treated with enalapril alone for up to 48 weeks, mean increases in serum potassium of approximately 0.2 mEq/L were observed. In patients treated with enalapril plus a thiazide diuretic, there was essentially no change in serum potassium (see PRECAUTIONS). Removal of angiotensin II negative feedback on renin secretion leads to increased plasma renin activity.

ACE is identical to kininase, an enzyme that degrades bradykinin. Whether increased levels of bradykinin, a potent vasodepressor peptide, play a role in the therapeutic effects of enalaprilat remains to be elucidated.

While the mechanism through which enalaprilat lowers blood pressure is believed to be primarily suppression of the renin-angiotensin-aldosterone system, enalaprilat has anti-hypertensive activity even in patients with low-renin hypertension. In clinical studies, black hypertensive patients (usually a low-renin hypertensive population) had a smaller average response to enalaprilat monotherapy than non-black patients.

Pharmacokinetics and Metabolism

Following intravenous administration of a single dose, the serum concentration profile of enalaprilat is polyexponential with a prolonged terminal phase, apparently representing a small fraction of the administered dose that has been bound to ACE. The amount bound does not increase with dose, indicating a saturable site of binding. The effective half-life for accumulation of enalaprilat, as determined from oral administration of multiple doses of enalapril maleate, is approximately 11 hours. Excretion of enalaprilat is primarily renal with more than 90 percent of an administered dose recovered in the urine as unchanged drug within 24 hours. Enalaprilat is poorly absorbed following oral administration.

The disposition of enalaprilat in patients with renal insufficiency is similar to that in patients with normal renal function until the glomerular filtration rate is 30 mL/min or less. With glomerular filtration rate ≤30 mL/min, peak and trough enalaprilat levels increase, time to peak concentration increases and time to steady state may be delayed. The effective half-life of enalaprilat is prolonged at this level of renal insufficiency (see DOSAGE AND ADMINISTRATION). Enalaprilat is dialyzable at the rate of 62 mL/min.

Studies in dogs indicate that enalaprilat does not enter the brain, and that enalapril crosses the blood-brain barrier poorly, if at all. Multiple doses of enalapril maleate in rats do not result in accumulation in any tissues. Milk in lactating rats contains radioactivity following administration of ^14C enalapril maleate. Radioactivity was found to cross the placenta following administration of labeled drug to pregnant hamsters.

Pharmacodynamics

Enalaprilat injection results in the reduction of both supine and standing systolic and diastolic blood pressure, usually with no orthostatic component. Symptomatic postural hypotension is therefore infrequent, although it might be anticipated in volume-depleted patients (see WARNINGS). The onset of action usually occurs within fifteen minutes of administration with the maximum effect occurring within one to four hours. The abrupt withdrawal of enalaprilat has not been associated with a rapid increase in blood pressure. The duration of hemodynamic effects appears to be dose-related. However, for the recommended dose, the duration of action in most patients is approximately six hours.

Following administration of enalapril, there is an increase in renal blood flow; glomerular filtration rate is usually unchanged. The effects appear to be similar in patients with renovascular hypertension.

In a clinical pharmacology study, indomethacin or sulindac was administered to hypertensive patients receiving enalapril maleate. In this study there was no evidence of a blunting of the antihypertensive action of enalapril maleate (see PRECAUTIONS, Drug Interactions).

INDICATIONS AND USAGE

Enalaprilat injection is indicated for the treatment of hypertension when oral therapy is not practical.

Enalaprilat injection has been studied with only one other antihypertensive agent, furosemide, which showed approximately additive effects on blood pressure. Enalapril, the pro-drug of enalaprilat, has been used extensively with a variety of other antihypertensive agents, without apparent difficulty except for occasional hypotension.

In using enalaprilat injection, consideration should be given to the fact that another angiotensin-converting enzyme inhibitor, captopril, has caused agranulocytosis, particularly in patients with renal impairment or collagen vascular disease, and that available data are insufficient to show that enalaprilat injection does not have a similar risk (see WARNINGS).

In considering use of enalaprilat, it should be noted that in controlled clinical trials ACE inhibitors have an effect on blood pressure that is less in black patients than in non-blacks. In addition, it should be noted that black patients receiving ACE inhibitors have been reported to have a higher incidence of angioedema compared to non-blacks (see WARNINGS, Angioedema).

CONTRAINDICATIONS

Enalaprilat injection is contraindicated in patients who are hypersensitive to any component of this product and in patients with a history of angioedema related to previous treatment with an angiotensin-converting enzyme inhibitor and in patients with hereditary or idiopathic angioedema.

WARNINGS

Hypotension

Excessive hypotension is rare in uncomplicated hypertensive patients but is a possible consequence of the use of enalaprilat especially in severely salt/volume depleted persons such as those treated vigorously with diuretics or patients on dialysis. Patients at risk for excessive hypotension, sometimes associated with oliguria and/or progressive azotemia, and rarely with acute renal failure and/or death, include those with the following conditions or characteristics: heart failure, hyponatremia, high dose diuretic therapy, recent intensive diuresis or increase in diuretic dose, renal dialysis, or severe volume and/or salt depletion of any etiology. It may be advisable to eliminate the diuretic, reduce the diuretic dose or increase salt intake cautiously before initiating therapy with enalaprilat injection in patients at risk for excessive hypotension who are able to tolerate such adjustments (see PRECAUTIONS, Drug Interactions; ADVERSE REACTIONS, and DOSAGE AND ADMINISTRATION). In patients with heart failure, with or without associated renal insufficiency, excessive hypotension has been observed and may be associated with oliguria and/or progressive azotemia, and rarely with acute renal failure and/or death. Because of the potential for an excessive fall in blood pressure especially in these patients, therapy should be followed closely whenever the dose of enalaprilat is adjusted and/or diuretic is increased. Similar considerations may apply to patients with ischemic heart or cerebrovascular disease, in whom an excessive fall in blood pressure could result in a myocardial infarction or cerebrovascular accident.

If hypotension occurs, the patient should be placed in the supine position and, if necessary, receive an intravenous infusion of normal saline. A transient hypotensive response is not a contraindication to further doses, which usually can be given without difficulty once the blood pressure has increased after volume expansion.

Anaphylactoid and Possibly Related Reactions

Presumably because angiotensin-converting enzyme inhibitors affect the metabolism of eicosanoids and polypeptides, including endogenous bradykinin, patients receiving ACE inhibitors (including enalaprilat injection) may be subject to a variety of adverse reactions, some of them serious.

Angioedema: Angioedema of the face, extremities, lips, tongue, glottis and/or larynx has been reported in patients treated with angiotensin-converting enzyme inhibitors, including enalaprilat. This may occur at any time during treatment. In such cases, enalaprilat injection should be promptly discontinued and appropriate therapy and monitoring should be provided until complete and sustained resolution of signs and symptoms has occurred. In instances where swelling has been confined to the face and lips, the condition has generally resolved without treatment, although antihistamines have been useful in relieving symptoms. Angioedema associated with laryngeal edema may be fatal. Where there is involvement of the tongue, glottis or larynx, likely to cause airway obstruction, appropriate therapy, e.g., subcutaneous epinephrine solution 1:1000 (0.3 mL to 0.5 mL) and/or measures necessary to ensure a patent airway, should be promptly provided (see ADVERSE REACTIONS).

Patients with a history of angioedema unrelated to ACE inhibitor therapy may be at increased risk of angioedema while receiving an ACE inhibitor (see also INDICATIONS AND USAGE and CONTRAINDICATIONS).

Anaphylactoid reactions during desensitization: Two patients undergoing desensitizing treatment with hymenoptera venom while receiving ACE inhibitors sustained life-threatening anaphylactoid reactions. In the same patients, these reactions were avoided when ACE inhibitors were temporarily withheld, but they reappeared upon inadvertent rechallenge.

Anaphylactoid reactions during membrane exposure: Anaphylactoid reactions have been reported in patients dialyzed with high-flux membranes and treated concomitantly with an ACE inhibitor. Anaphylactoid reactions have also been reported in patients undergoing low-density lipoprotein apheresis with dextran sulfate absorption.

Neutropenia/Agranulocytosis

Another angiotensin-converting enzyme inhibitor, captopril, has been shown to cause agranulocytosis and bone marrow depression, rarely in uncomplicated patients but more frequently in patients with renal impairment especially if they also have a collagen vascular disease. Available data from clinical trials of enalapril are insufficient to show that enalapril does not cause agranulocytosis in similar rates. Marketing experience has revealed cases of neutropenia, or agranulocytosis in which a causal relationship to enalapril cannot be excluded. Periodic monitoring of white blood cell counts in patients with collagen vascular disease and renal disease should be considered.

Hepatic Failure

Rarely, ACE inhibitors have been associated with a syndrome that starts with cholestatic jaundice and progresses to fulminant hepatic necrosis, and (sometimes) death. The mechanism of this syndrome is not understood. Patients receiving ACE inhibitors who develop jaundice or marked elevations of hepatic enzymes should discontinue the ACE inhibitor and receive appropriate medical follow-up.

Fetal/Neonatal Morbidity and Mortality

ACE inhibitors can cause fetal and neonatal morbidity and death when administered to pregnant women. Several dozen cases have been reported in the world literature. When pregnancy is detected, ACE inhibitors should be discontinued as soon as possible.

The use of ACE inhibitors during the second and third trimesters of pregnancy has been associated with fetal and neonatal injury, including hypotension, neonatal skull hypoplasia, anuria, reversible or irreversible renal failure, and death. Oligohydramnios has also been reported, presumably resulting from decreased fetal renal function; oligohydramnios in this setting has been associated with fetal limb contractures, craniofacial deformation, and hypoplastic lung development. Prematurity, intrauterine growth retardation, and patent ductus arteriosus have also been reported, although it is not clear whether these occurrences were due to the ACE-inhibitor exposure.

These adverse effects do not appear to have resulted from intrauterine ACE-inhibitor exposure that has been limited to the first trimester. Mothers whose embryos and fetuses are exposed to ACE inhibitors only during the first trimester should be so informed. Nonetheless, when patients become pregnant, physicians should make every effort to discontinue the use of enalaprilat injection as soon as possible.

Rarely (probably less often than once in every thousand pregnancies), no alternative to ACE inhibitors will be found. In these rare cases, the mothers should be apprised of the potential hazards to their fetuses, and serial ultrasound examinations should be performed to assess the intraamniotic environment.

If oligohydramnios is observed, enalaprilat injection should be discontinued unless it is considered lifesaving for the mother. Contraction stress testing (CST), a non-stress test (NST), or biophysical profiling (BPP) may be appropriate, depending upon the week of pregnancy. Patients and physicians should be aware, however, that oligohydramnios may not appear until after the fetus has sustained irreversible injury.

Infants with histories of in utero exposure to ACE inhibitors should be closely observed for hypotension, oliguria, and hyperkalemia. If oliguria occurs, attention should be directed toward support of blood pressure and renal perfusion. Exchange transfusion or dialysis may be required as means of reversing hypotension and/or substituting for disordered renal function. Enalapril, which crosses the placenta, has been removed from neonatal circulation by peritoneal dialysis with some clinical benefit, and theoretically may be removed by exchange transfusion, although there is no experience with the latter procedure.

No teratogenic effects of oral enalapril were seen in studies of pregnant rats and rabbits. On a body surface area basis, the doses used were 57 times and 12 times, respectively, the maximum recommended human daily dose (MRHDD).

PRECAUTIONS

General

Aortic Stenosis/Hypertrophic Cardiomyopathy: As with all vasodilators, enalapril should be given with caution to patients with obstruction in the outflow tract of the left ventricle.

Impaired Renal Function: As a consequence of inhibiting the renin-angiotensin-aldosterone system, changes in renal function may be anticipated in susceptible individuals. In patients with severe heart failure whose renal function may depend on the activity of the renin-angiotensin-aldosterone system, treatment with angiotensin-converting enzyme inhibitors, including enalapril or enalaprilat, may be associated with oliguria and/or progressive azotemia and rarely with acute renal failure and/or death.

In clinical studies in hypertensive patients with unilateral or bilateral renal artery stenosis, increases in blood urea nitrogen and serum creatinine were observed in 20 percent of patients receiving enalapril. These increases were almost always reversible upon discontinuation of enalapril or enalaprilat and/or diuretic therapy. In such patients renal function should be monitored during the first few weeks of therapy.

Some hypertensive patients with no apparent pre-existing renal vascular disease have developed increases in blood urea and serum creatinine, usually minor and transient, especially when enalaprilat has been given concomitantly with a diuretic. This is more likely to occur in patients with pre-existing renal impairment. Dosage reduction of enalaprilat and/or discontinuation of the diuretic may be required.

Evaluation of the hypertensive patient should always include assessment of renal function (see DOSAGE AND ADMINISTRATION).

Hyperkalemia: Elevated serum potassium (greater than 5.7 mEq/L) was observed in approximately one percent of hypertensive patients in clinical trials receiving enalapril. In most cases these were isolated values which resolved despite continued therapy. Hyperkalemia was a cause of discontinuation of therapy in 0.28 percent of hypertensive patients. Risk factors for the development of hyperkalemia include renal insufficiency, diabetes mellitus, and the concomitant use of potassium-sparing agents or potassium supplements, which should be used cautiously, if at all, with enalaprilat injection (see Drug Interactions).

Cough: Presumably due to the inhibition of the degradation of endogenous bradykinin, persistent nonproductive cough has been reported with all ACE inhibitors, always resolving after discontinuation of therapy. ACE inhibitor-induced cough should be considered in the differential diagnosis of cough.

Surgery/Anesthesia: In patients undergoing major surgery or during anesthesia with agents that produce hypotension, enalapril may block angiotensin II formation secondary to compensatory renin release. If hypotension occurs and is considered to be due to this mechanism, it can be corrected by volume expansion.

Drug Interactions

Hypotension-Patients on Diuretic Therapy: Patients on diuretics and especially those in whom diuretic therapy was recently instituted, may occasionally experience an excessive reduction of blood pressure after initiation of therapy with enalaprilat. The possibility of hypotensive effects with enalaprilat can be minimized by administration of an intravenous infusion of normal saline, discontinuing the diuretic or increasing the salt intake prior to initiation of treatment with enalaprilat. If it is necessary to continue the diuretic, provide close medical supervision for at least one hour after the initial dose of enalaprilat (see WARNINGS).

Agents Causing Renin Release: The antihypertensive effect of enalaprilat injection appears to be augmented by antihypertensive agents that cause renin release (e.g., diuretics).

Non-Steroidal Anti-Inflammatory Agents: In some patients with compromised renal function who are being treated with non-steroidal anti-inflammatory drugs, the coadministration of enalapril may result in a further deterioration of renal function. These effects are usually reversible.

In a clinical pharmacology study, indomethacin or sulindac was administered to hypertensive patients receiving enalapril maleate. In this study there was no evidence of a blunting of the antihypertensive action of enalapril maleate. However, reports suggest that NSAIDs may diminish the antihypertensive effect of ACE inhibitors. This interaction should be given consideration in patients taking NSAIDs concomitantly with ACE inhibitors.

Other Cardiovascular Agents: Enalaprilat injection has been used concomitantly with digitalis, beta adrenergic-blocking agents, methyldopa, nitrates, calcium-blocking agents, hydralazine and prazosin without evidence of clinically significant adverse interactions.

Agents Increasing Serum Potassium: Enalaprilat injection attenuates potassium loss caused by thiazide-type diuretics. Potassium-sparing diuretics (e.g., spironolactone, triamterene, or amiloride), potassium supplements, or potassium-containing salt substitutes may lead to significant increases in serum potassium. Therefore, if concomitant use of these agents is indicated because of demonstrated hypokalemia, they should be used with caution and with frequent monitoring of serum potassium.

Lithium: Lithium toxicity has been reported in patients receiving lithium concomitantly with drugs which cause elimination of sodium, including ACE inhibitors. A few cases of lithium toxicity have been reported in patients receiving concomitant enalapril and lithium and were reversible upon discontinuation of both drugs. It is recommended that serum lithium levels be monitored frequently if enalapril is administered concomitantly with lithium.

Gold: Nitritoid reactions (symptoms include facial flushing, nausea, vomiting and hypotension) have been reported rarely in patients on therapy with injectable gold (sodium aurothiomalate) and concomitant ACE inhibitor therapy.

Carcinogenesis, Mutagenesis, Impairment of Fertility

Carcinogenicity studies have not been done with enalaprilat injection.

Enalaprilat injection is the bioactive form of its ethyl ester, enalapril maleate. There was no evidence of a tumorigenic effect when enalapril was administered for 106 weeks to male and female rats at doses up to 90 mg/kg/day or for 94 weeks to male and female mice at doses up to 90 and 180 mg/kg/day, respectively. These doses are 26 times (in rats and female mice) and 13 times (in male mice) the maximum recommended human daily dose (MRHDD) when compared on a body surface area basis.

Enalaprilat injection was not mutagenic in the Ames microbial mutagen test with or without metabolic activation. Enalapril showed no drug-related changes in the following genotoxicity studies: rec-assay, reverse mutation assay with E. coli, sister chromatid exchange with cultured mammalian cells, the micronucleus test with mice, and in an in vivo cytogenic study using mouse bone marrow. There were no adverse effects on reproductive performance of male and female rats treated with up to 90 mg/kg/day of enalapril (26 times the MRHDD when compared on a body surface area basis).

Pregnancy

Pregnancy Categories C (first trimester) and D (second and third trimesters) See WARNINGS, Fetal/Neonatal Morbidity and Mortality.

Nursing Mothers

Enalapril and enalaprilat have been detected in human breast milk. Because of the potential for serious adverse reactions in nursing infants from enalapril, a decision should be made whether to discontinue nursing or to discontinue enalaprilat injection, taking into account the importance of the drug to the mother.

Pediatric Use

Safety and effectiveness in pediatric patients have not been established.

Geriatric Use

Clinical studies of enalaprilat did not include sufficient numbers of subjects aged 65 and over to determine whether they respond differently from younger subjects. Other reported clinical experience has not identified differences in responses between the elderly and younger patients. In general, dose selection for an elderly patient should be cautious, usually starting at the low end of the dosing range, reflecting the greater frequency of decreased hepatic, renal, or cardiac function, and of concomitant disease or other drug therapy.

This drug is known to be substantially excreted by the kidney, and the risk of toxic reactions to this drug may be greater in patients with impaired renal function. Because elderly patients are more likely to have decreased renal function, care should be taken in dose selection. Evaluation of the hypertensive patient should always include assessment of renal function (see DOSAGE AND ADMINISTRATION).

ADVERSE REACTIONS

Enalaprilat has been found to be generally well tolerated in controlled clinical trials involving 349 patients (168 with hypertension, 153 with congestive heart failure and 28 with coronary artery disease). The most frequent clinically significant adverse experience was hypotension (3.4 percent), occurring in eight patients (5.2 percent) with congestive heart failure, three (1.8 percent) with hypertension and one with coronary artery disease. Other adverse experiences occurring in greater than one percent of patients were: headache (2.9 percent) and nausea (1.1 percent).

Adverse experiences occurring in 0.5 to 1 percent of patients in controlled clinical trials included: myocardial infarction, fatigue, dizziness, fever, rash and constipation.

Angioedema: Angioedema has been reported in patients receiving enalaprilat, with an incidence higher in black than in non-black patients. Angioedema associated with laryngeal edema may be fatal. If angioedema of the face, extremities, lips, tongue, glottis and/or larynx occurs, treatment with enalaprilat should be discontinued and appropriate therapy instituted immediately (see WARNINGS).

Cough: See PRECAUTIONS, Cough.

Enalapril Maleate

Since enalapril is converted to enalaprilat, those adverse experiences associated with enalapril might also be expected to occur with enalaprilat injection.

The following adverse experiences have been reported with enalapril and, within each category, are listed in order of decreasing severity.

Body as a Whole: Syncope, orthostatic effects, anaphylactoid reactions (see WARNINGS, Anaphylactoid reactions during membrane exposure), chest pain, abdominal pain, asthenia.

Cardiovascular: Cardiac arrest; myocardial infarction or cerebrovascular accident, possibly secondary to excessive hypotension in high risk patients (see WARNINGS,Hypotension); pulmonary embolism and infarction; pulmonary edema; rhythm disturbances including atrial tachycardia and bradycardia; atrial fibrillation; orthostatic hypotension; angina pectoris; palpitation, Raynaud's phenomenon.

Digestive: Ileus, pancreatitis, hepatic failure, hepatitis (hepatocellular [proven on rechallenge] or cholestatic jaundice) (see WARNINGS, Hepatic Failure), melena, diarrhea, vomiting, dyspepsia, anorexia, glossitis, stomatitis, dry mouth.

Hematologic: Rare cases of neutropenia, thrombocytopenia and bone marrow depression.

Musculoskeletal: Muscle cramps.

Nervous/Psychiatric: Depression, vertigo, confusion, ataxia, somnolence, insomnia, nervousness, peripheral neuropathy (e.g., paresthesia, dysesthesia), dream abnormality.

Respiratory: Bronchospasm, dyspnea, pneumonia, bronchitis, cough, rhinorrhea, sore throat and hoarseness, asthma, upper respiratory infection, pulmonary infiltrates, eosinophilic pneumonitis.

Skin: Exfoliative dermatitis, toxic epidermal necrolysis, Stevens-Johnson syndrome, pemphigus, herpes zoster, erythema multiforme, urticaria, pruritus, alopecia, flushing, diaphoresis, photosensitivity.

Special Senses: Blurred vision, taste alteration, anosmia, tinnitus, conjunctivitis, dry eyes, tearing.

Urogenital: Renal failure, oliguria, renal dysfunction (see PRECAUTIONS and DOSAGE AND ADMINISTRATION), urinary tract infection, flank pain, gynecomastia, impotence.

Miscellaneous: A symptom complex has been reported which may include some or all of the following: a positive ANA, an elevated erythrocyte sedimentation rate, arthralgia/arthritis, myalgia/myositis, fever, serositis, vasculitis, leukocytosis, eosinophilia, photosensitivity, rash and other dermatologic manifestations.

Hypotension: Combining the results of clinical trials in patients with hypertension or congestive heart failure, hypotension (including postural hypotension, and other orthostatic effects) was reported in 2.3 percent of patients following the initial dose of enalapril or during extended therapy. In the hypertensive patients, hypotension occurred in 0.9 percent and syncope occurred in 0.5 percent of patients. Hypotension or syncope was a cause for discontinuation of therapy in 0.1 percent of hypertensive patients (see WARNINGS).

Fetal/Neonatal Morbidity and Mortality: See WARNINGS, Fetal/Neonatal Morbidity and Mortality.

Clinical Laboratory Test Findings

Serum Electrolytes: Hyperkalemia (see PRECAUTIONS), hyponatremia.

Creatinine, Blood Urea Nitrogen: In controlled clinical trials minor increases in blood urea nitrogen and serum creatinine, reversible upon discontinuation of therapy, were observed in about 0.2 percent of patients with essential hypertension treated with enalapril alone. Increases are more likely to occur in patients receiving concomitant diuretics or in patients with renal artery stenosis (see PRECAUTIONS).

Hematology: Small decreases in hemoglobin and hematocrit (mean decreases of approximately 0.3 g percent and 1 vol percent, respectively) occur frequently in hypertensive patients treated with enalapril but are rarely of clinical importance unless another cause of anemia coexists. In clinical trials, less than 0.1 percent of patients discontinued therapy due to anemia. Hemolytic anemia, including cases of hemolysis in patients with G-6-PD deficiency, has been reported; a causal relationship to enalapril cannot be excluded.

Liver Function Tests: Elevations of liver enzymes and/or serum bilirubin have occurred (see WARNINGS, Hepatic Failure).

OVERDOSAGE

In clinical studies, some hypertensive patients received a maximum dose of 80 mg of enalaprilat intravenously over a fifteen minute period. At this high dose, no adverse effects beyond those as associated with the recommended dosages were observed.

A single intravenous dose of ≤4,167 mg/kg of enalaprilat was associated with lethality in female mice. No lethality occurred after an intravenous dose of 3,472 mg/kg. The most likely manifestation of overdosage would be hypotension, for which the usual treatment would be intravenous infusion of normal saline solution.

Enalaprilat may be removed from general circulation by hemodialysis and has been removed from neonatal circulation by peritoneal dialysis (see WARNINGS, Anaphylactoid reactions during membrane exposure).

DOSAGE AND ADMINISTRATION

FOR INTRAVENOUS ADMINISTRATION ONLY

The dose in hypertension is 1.25 mg every six hours administered intravenously over a five minute period. A clinical response is usually seen within 15 minutes. Peak effects after the first dose may not occur for up to four hours after dosing. The peak effects of the second and subsequent doses may exceed those of the first.

No dosage regimen for enalaprilat injection has been clearly demonstrated to be more effective in treating hypertension than 1.25 mg every six hours. However, in controlled clinical studies in hypertension, doses as high as 5 mg every six hours were well tolerated for up to 36 hours. There has been inadequate experience with doses greater than 20 mg per day.

In studies of patients with hypertension, enalaprilat has not been administered for periods longer than 48 hours. In other studies, patients have received enalaprilat for as long as seven days.

The dose for patients being converted to enalaprilat injection from oral therapy for hypertension with enalapril maleate is 1.25 mg every six hours. For conversion from intravenous to oral therapy, the recommended initial dose of oral enalapril maleate, is 5 mg once a day with subsequent dosage adjustments as necessary.

Patients On Diuretic Therapy

For patients on diuretic therapy the recommended starting dose for hypertension is 0.625 mg administered intravenously over a five minute period; also see below, Patients at Risk of Excessive Hypotension. A clinical response is usually seen within 15 minutes. Peak effects after the first dose may not occur for up to four hours after dosing, although most of the effect is usually apparent within the first hour. If after one hour there is an inadequate clinical response, the 0.625 mg dose may be repeated. Additional doses of 1.25 mg may be administered at six hour intervals.

For conversion from intravenous to oral therapy, the recommended initial dose of oral enalapril maleate for patients who have responded to 0.625 mg of enalaprilat every six hours is 2.5 mg once a day with subsequent dosage adjustment as necessary.

Dosage Adjustment in Renal Impairment

The usual dose of 1.25 mg of enalaprilat injection every six hours is recommended for patients with a creatinine clearance > 30 mL/min (serum creatinine of up to approximately 3 mg/dL). For patients with creatinine clearance ≤ 30 mL/min (serum creatinine ≥ 3 mg/dL), the initial dose is 0.625 mg (see WARNINGS).

If after one hour there is an inadequate clinical response, the 0.625 mg dose may be repeated. Additional doses of 1.25 mg may be administered at six hour intervals.

For dialysis patients, see below, Patients at Risk of Excessive Hypotension.

For conversion from intravenous to oral therapy, the recommended initial dose of oral enalapril maleate is 5 mg once a day for patients with creatinine clearance > 30 mL/min and 2.5 mg once daily for patients with creatinine clearance ≤ 30 mL/min. Dosage should then be adjusted according to blood pressure response.

Patients at Risk of Excessive Hypotension

Hypertensive patients at risk of excessive hypotension include those with the following concurrent conditions or characteristics: heart failure, hyponatremia, high dose diuretic therapy, recent intensive diuresis or increase in diuretic dose, renal dialysis, or severe volume and/or salt depletion of any etiology (see WARNINGS). Single doses of enalaprilat injection as low as 0.2 mg have produced excessive hypotension in normotensive patients with these diagnoses. Because of the potential for an extreme hypotensive response in these patients, therapy should be started under very close medical supervision. The starting dose should be no greater than 0.625 mg administered intravenously over a period of no less than five minutes and preferably longer (up to one hour).

Patients should be followed closely whenever the dose of enalaprilat injection is adjusted and/or diuretic is increased.

Administration

Enalaprilat injection should be administered as a slow intravenous infusion, as indicated above. It may be administered as provided or diluted with up to 50 mL of a compatible diluent.

Parenteral drug products should be inspected visually for particulate matter and discoloration prior to use whenever solution and container permit.

Compatibility and Stability

Enalaprilat injection as supplied and mixed with the following intravenous diluents has been found to maintain full activity for 24 hours at room temperature:

5 percent Dextrose Injection

0.9 percent Sodium Chloride Injection

0.9 percent Sodium Chloride Injection in 5 percent Dextrose

5 percent Dextrose in Lactated Ringer's Injection

ISOLYTE***E (*** Registered trademark of B. Braun)

HOW SUPPLIED

Enalaprilat Injection USP, 1.25 mg/mL is a clear, colorless solution free from visible particulate matter and is available as follows:

Enalaprilat Injection USP, 1.25 mg/mL | NDC 43598-078-58 | 10 vials per carton
Enalaprilat Injection USP, 2.5 mg/2 mL | NDC 43598-169-58 | 10 vials per carton

Storage

Store at 20°C to 25°C (68°F to 77°F) [See USP Controlled Room Temperature].

To report SUSPECTED ADVERSE REACTIONS, contact Dr. Reddy’s Laboratories Inc., at 1-888-375-3784 or FDA at 1-800-FDA-1088 or www.fda.gov/medwatch.

Distributor:

Dr. Reddy’s Laboratories Inc.,

Princeton, NJ 08540

Made in India

Revised: 04/2023

PACKAGE LABEL PRINCIPAL DISPLAY PANEL SECTION

Enalaprilat Injection, USP 1.25 mg/mL - Vial Label

PACKAGE LABEL

Enalaprilat Injection, USP 1.25 mg/mL - Carton Label - 10 x 1 mL Single-Dose Vials

PACKAGE LABEL

Enalaprilat Injection, USP 2.5 mg/2 mL - Vial Label

PACKAGE LABEL

Enalaprilat Injection, USP 2.5 mg/2 mL (1.25 mg/mL) - Carton Label - 10 x 2 mL Single-Dose Vials